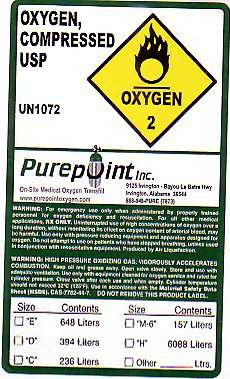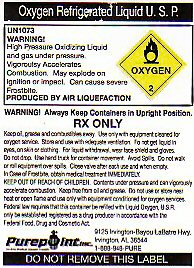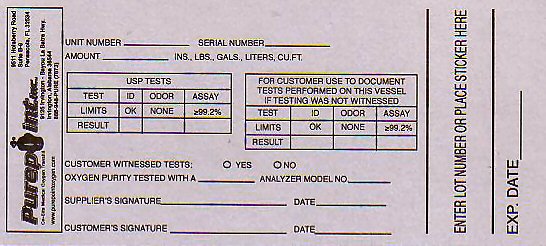 DRUG LABEL: OXYGEN
NDC: 46088-010 | Form: GAS
Manufacturer: Purepoint, Inc
Category: prescription | Type: HUMAN PRESCRIPTION DRUG LABEL
Date: 20110824

ACTIVE INGREDIENTS: OXYGEN 99 L/100 L

OXYGEN COMPRESSED USP LABEL

OXYGEN COMPRESSED USP UN1072 C.A.S. NO. 7782-44-7 OXYGEN-2 WARNING: HIGH PRESSURE OXIDIZING GAS. VIGOROUSLY ACCELERATES COMBUSTION. NO SMOKING IN THE PRESENCE OF OXYGEN OR A FIRE MAY RESULT. KEEP OIL AND GREASE AWAY. OPEN VALVE SLOWLY. STORE AND USE WITH ADEQUATE VENTILATION. USE ONLY WITH EQUIPMENT CLEANED FOR OXYGEN SERVICE AND RATED FOR CYLINDER PRESSURE. USE A BACK FLOW PREVENTATIVE DEVICE IN THE PIPING. CLOSE VALVE AFTER EACH USE AND WHEN EMPTY. CYLINDER TEMPERATURE SHOULD NOT EXCEED 52 C (125 F) USE IN ACCORDANCE WITH THE MATERIAL SAFETY DATA SHEET (MSDS) DO NOT REMOVE THIS PRODUCT LABEL.
WARNING: FOR EMERGENCY USE ONLY WHEN ADMINISTERED BY PROPERLY TRAINED PERSONNEL FOR OXYGEN DEFICIENCY AND RESUSCITATION. FOR ALL OTHER MEDICAL APPLICATIONS Rx ONLY. UNINTERRUPTED USE OF HIGH CONCENTRATIONS OF OXYGEN OVER A LONG DURATION WITHOUT MONITORING ITS EFFECT ON OXYGEN CONTENT OF ARTERIAL BLOOD MAY BE HARMFUL. USE ONLY WITH PRESSURE REDUCING EQUIPMENT AND APPARATUS DESIGNED FOR OXYGEN. DO NOT ATTEMPT TO USE ON PATIENTS WHO HAVE STOPPED BREATHING UNLESS USED IN CONJUNCTION WITH RESUSCITATIVE EQUIPMENT. PRODUCED BY AIR LIQUEFACTION.

OXYGEN REFRIGERATED LIQUID USP LABEL

OXYGEN REFRIGERATED LIQUID USP UN1073 ALWAYS KEEP CONTAINER IN UPRIGHT POSITION. EXTREMELY COLD LIQUID AND GAS UNDER PRESSURE. VIGOROUSLY ACCELERATES COMBUSTION. MAY EXPLODE ON IGNITION OR IMPACT. CAN CAUSE SEVERE FROSTBITE. KEEP OIL, GREASE AND COMBUSTIBLES AWAY. USE ONLY WITH EQUIPMENT CLEANED FOR OXYGEN SERVICE. STORE AND USE WITH ADEQUATE VENTILATION. DO NOT GET LIQUID IN EYES, ON SKIN OR CLOTHING. FOR LIQUID WITHDRAWAL, WEAR FACE SHIELD AND GLOVES. DO NOT DROP. USE HAND TRUCK FOR CONTAINER MOVEMENT. AVOID SPILLS. DO NOT WALK OR ROLL EQUIPMENT OVER SPILLS CLOSE VALVE AFTER EACH USE AND WHEN EMPTY.
FIRST AID: IN CASE OF FROSTBITE OBTAIN MEDICAL TREATMENT IMMEDIATELY.
KEEP OUT OF THE REACH OF CHILDREN. DO NOT USE OR STORE NEAR HEAT OR OPEN FLAME. FEDERAL LAW REQUIRES THAT THIS CONTAINER BE REFILLED WITH LIQUID OXYGEN USP ONLY BE ESTABLISHED REGISTERED AS A DRUG PRODUCER IN ACCORDANCE WITH THE FEDERAL FOOD DRUG AND COSMETIC ACT. PRODUCED BY AIR LIQUEFACTION. DO NOT REMOVE THIS PRODUCT LABEL.
LOT NUMBER_____________ SERIAL NUMBER__________ AMOUNT__________INS, LBS., GALS., LITERS, CU. FT.
USP TESTS
TEST ID ODOR ASSAY
LIMITS OK NONE LESS THAN 99.2%
RESULT
FOR CUSTOMER TO USE TO DOCUMENT TESTS PERFORMED ON THIS VESSEL
METHOD OF ANALYSIS FOR ASSAY IS THE PARAMAGNETIC OXYGEN ANALYZER MANUFACTURER__________ MODEL______________ CUSTOMER WITNESSED TESTS YES NO SUPPLIERS SIGNATURE__________ DATE____________ CUSTOMERS SIGNATURE_______________ DATE________________
LIQUID MEDICAL GASES LIQUID OXYGEN DELIVERY TAG FILLED AND DISTRIBUTED BY____________ THIS VESSEL CONTAINS OXYGEN USP (SEE REVERSE SIDE FOR TEST RESULTS) OXYGEN PRODUCED BY THE AIR LIQUEFACTION PROCESS